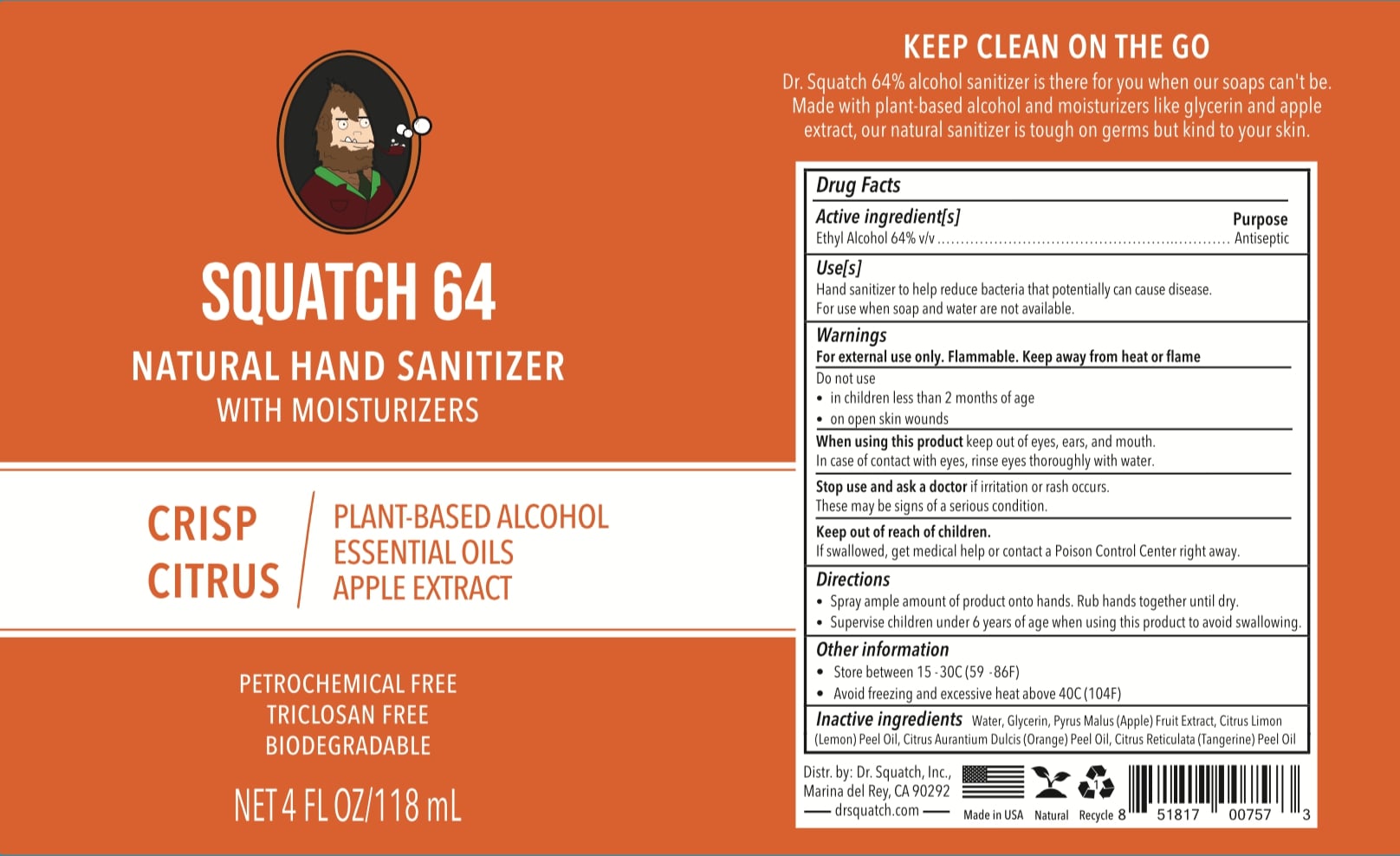 DRUG LABEL: Squatch 64 Natural Hand Sanitizer Crisp Citrus
NDC: 79151-001 | Form: SOLUTION
Manufacturer: Dr Squatch, Inc.
Category: otc | Type: HUMAN OTC DRUG LABEL
Date: 20211025

ACTIVE INGREDIENTS: ALCOHOL 64 mL/100 mL
INACTIVE INGREDIENTS: ORANGE OIL; LEMON OIL; MANDARIN OIL; GLYCERIN; APPLE; WATER

Squatch 64 Natural Hand Sanitizer Crisp Citrus

Active Ingredient(s)

Alcohol 64% v/v. Purpose: Antiseptic

PURPOSE

Hand Sanitizer to help reduce bacteria that potentially can cause disease. For use when soap and water are not available.

Keep out of reach of children. If swallowed, get medical help or contact a Poison Control Center right away.

Stop use and ask a doctor If irritation or rash occurs. These may be signs of a serious condition.

Warnings

For external use only. Flammable. Keep away from heat or flame

Do not use

- in children less than 2 months of age
- on open skin wounds

When using this product keep out of eyes, ears, and mouth. In case of contact with eyes, rinse eyes thoroughly with water.

Directions

- Spray ample amount of product onto hands. Rub hands together until dry.
- Supervise children under 6 years of age when using this product to avoid swallowing.

Other information

- Store between 15-30C (59-86F)
- Avoid freezing and excessive heat above 40C (104F)

INACTIVE INGREDIENT

Inactive ingredients Water, Glycerin, Pyrus Malus (Apple) Fruit Extract, Citrus Limon (Lemon) Peel Oil, Citrus Aurantium Dulcis (Orange) Peel Oil, Citrus Reticulata (Tangerine) Peel Oil.

PACKAGE LABEL

Squatch 64

Natural Hand Sanitizer with Moisturizers

Crisp Citrus

Plant-Based Alcohol

Essentail Oils

Apple Extract

Petrochemical Free

Triclosan Free

Biodegradable

Net 4 FL OZ/ 118 mL